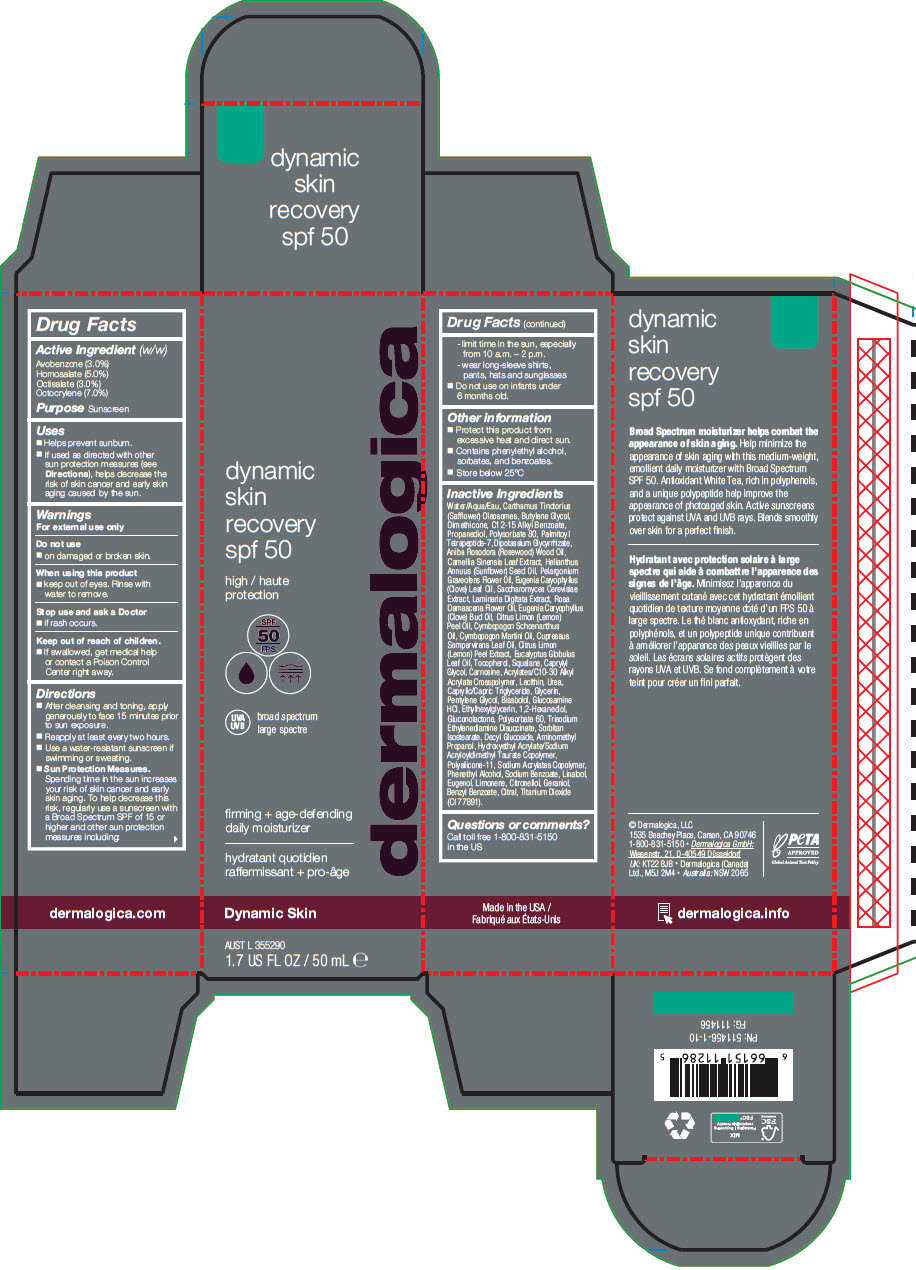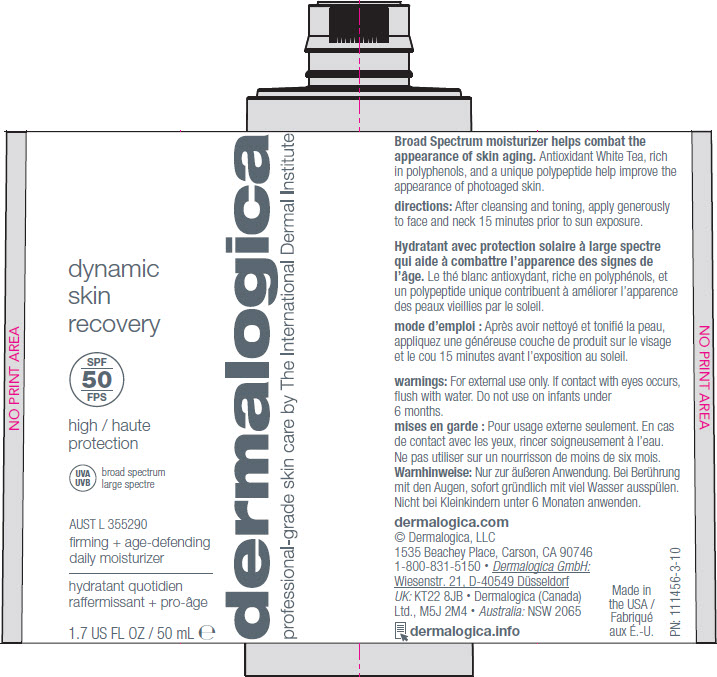 DRUG LABEL: dermalogica dynamic skin recovery spf 50
NDC: 68479-382 | Form: LOTION
Manufacturer: Dermalogica, LLC
Category: otc | Type: HUMAN OTC DRUG LABEL
Date: 20241017

ACTIVE INGREDIENTS: AVOBENZONE 3 g/100 mL; HOMOSALATE 5 g/100 mL; OCTISALATE 3 g/100 mL; OCTOCRYLENE 7 g/100 mL
INACTIVE INGREDIENTS: PELARGONIUM GRAVEOLENS FLOWER OIL; CLOVE LEAF OIL; LAMINARIA DIGITATA; SACCHAROMYCES CEREVISIAE; ROSA X DAMASCENA FLOWER OIL; CLOVE OIL; LEMON OIL, COLD PRESSED; CUPRESSUS SEMPERVIRENS LEAF OIL; PALMAROSA OIL; CYMBOPOGON SCHOENANTHUS OIL; LEMON PEEL; EUCALYPTUS OIL; SUNFLOWER OIL; TOCOPHEROL; SQUALANE; CAPRYLYL GLYCOL; CARBOMER INTERPOLYMER TYPE A (ALLYL SUCROSE CROSSLINKED); CARNOSINE; SOYBEAN LECITHIN; UREA; CAPRYLIC/CAPRIC/LAURIC TRIGLYCERIDE; GLYCERIN; PENTYLENE GLYCOL; .ALPHA.-BISABOLOL, (+)-; GLUCOSAMINE HYDROCHLORIDE; ETHYLHEXYLGLYCERIN; 1,2-HEXANEDIOL; TITANIUM DIOXIDE; GLUCONOLACTONE; POLYSORBATE 60; TRISODIUM ETHYLENEDIAMINE DISUCCINATE; SORBITAN ISOSTEARATE; DECYL GLUCOSIDE; AMINOMETHYLPROPANOL; HYDROXYETHYL ACRYLATE/SODIUM ACRYLOYLDIMETHYL TAURATE COPOLYMER (100000 MPA.S AT 1.5%); DIMETHICONE/VINYL DIMETHICONE CROSSPOLYMER (SOFT PARTICLE); SODIUM ACRYLATE/STYRENE SULFONATE COPOLYMER (11000 MW); PHENYLETHYL ALCOHOL; SODIUM BENZOATE; LINALOOL, (+)-; EUGENOL; LIMONENE, (+)-; .BETA.-CITRONELLOL, (+/-)-; GERANIOL; BENZYL BENZOATE; CITRAL; WATER; CARTHAMUS TINCTORIUS SEED OLEOSOMES; BUTYLENE GLYCOL; DIMETHICONE; ALKYL (C12-15) BENZOATE; PROPANEDIOL; POLYSORBATE 80; PALMITOYL TETRAPEPTIDE-7; GLYCYRRHIZINATE DIPOTASSIUM; ROSEWOOD OIL; GREEN TEA LEAF; ACRYLATES/C10-30 ALKYL ACRYLATE CROSSPOLYMER (60000 MPA.S)

dermalogica
dynamic skin recovery spf 50

Active ingredients

Avobenzone (3.0%)
Homosalate (5.0%)
Octisalate (3.0%)
Octocrylene (7.0%)

Purpose

Sunscreen

Uses

Helps prevent sunburn.
If used as directed with other
sun protection measures (see
Directions), helps decrease
the risk of skin cancer and early
skin aging caused by the sun.

Warnings

For external use only

Do not use

on damaged or broken skin.

When using this product

keep out of eyes. Rinse with
water to remove.

Stop use and ask a doctor

if rash occurs.

Keep out of reach of children.

If swallowed, get medical help
or contact a Poison Control
Center right away.

Directions

Apply liberally 30 minutes before
sun exposure
Reapply at least every two hours
Use a water-resistant sunscreen if
swimming or sweating
Sun Protection Measures.
Spending time in the sun
increases your risk of skin cancer
and early skin aging. To help
decrease this risk, regularly use a
sunscreen with a Broad Spectrum
SPF of 15 or higher and other sun
protection measures including:
- limit time in the sun, especially
from 10 a.m. – 2 p.m.

- wear long-sleeve
shirts, pants, hats and
sunglasses
Do not use on infants
under 6 months old.

Other information

Protect this product
from excessive heat
and direct sun.

Inactive ingredients

Water/Aqua/Eau, Carthamus Tinctorius
(Safflower) Oleosomes, Butylene
Glycol, Dimethicone, C12-15 Alkyl
Benzoate, Propanediol, Polysorbate 80,
Palmitoyl Tetrapeptide-7, Dipotassium
Glycyrrhizate, Aniba Rosodora (Rosewood)
Wood Oil, Camellia Sinensis Leaf Extract,
Helianthus Annuus (Sunflower) Seed
Oil, Pelargonium Graveolens Flower
Oil, Eugenia Caryophyllus (Clove)
Leaf Oil, Saccharomyces Cerevisiae
Extract, Laminaria Digitata Extract,
Rosa Damascena Flower Oil, Eugenia
Caryophyllus (Clove) Bud Oil, Citrus
Limon (Lemon) Peel Oil, Cymbopogon
Schoenanthus Oil, Cymbopogon
Martini Oil, Cupressus Sempervirens
Leaf Oil, Citrus Limon (Lemon) Peel
Extract, Eucalyptus Globulus Leaf Oil,
Tocopherol, Squalane, Caprylyl Glycol,
Carnosine, Acrylates/C10-30 Alkyl
Acrylate Crosspolymer, Lecithin, Urea,
Caprylic/Capric Triglyceride, Glycerin,
Pentylene Glycol, Bisabolol, Glucosamine
HCl, Ethylhexylglycerin, 1,2-Hexanediol,
Gluconolactone, Polysorbate 60,
Trisodium Ethylenediamine Disuccinate,
Sorbitan Isostearate, Decyl Glucoside,
Aminomethyl Propanol, Hydroxyethyl
Acrylate/Sodium Acryloyldimethyl Taurate
Copolymer, Polysilicone-11, Sodium
Acrylates Copolymer, Phenethyl Alcohol,
Sodium Benzoate, Linalool, Eugenol,
Limonene, Citronellol, Geraniol, Benzyl
Benzoate, Citral, Titanium Dioxide
(CI 77891).

Questions or comments?

Call toll free
1-800-831-5150 in the US.

PRINCIPAL DISPLAY PANEL - 50 mL Bottle Carton

dermalogica

dynamic
skin
recovery
spf 50

high
protection

SPF
50

UVA
UVB
broad spectrum

firming + age-defending
daily moisturizer

Dynamic Skin

AUST L 355290
1.7 US FL OZ / 50 mL ℮

PRINCIPAL DISPLAY PANEL - 50 mL Bottle Label

dermalogica
professional-grade skin care by The International Dermal Institute

dynamic
skin
recovery

SPF
50

high
protection

UVA
UVB
broad spectrum

AUST L 355290
firming + age-defending
daily moisturizer

1.7 US FL OZ / 50 mL ℮